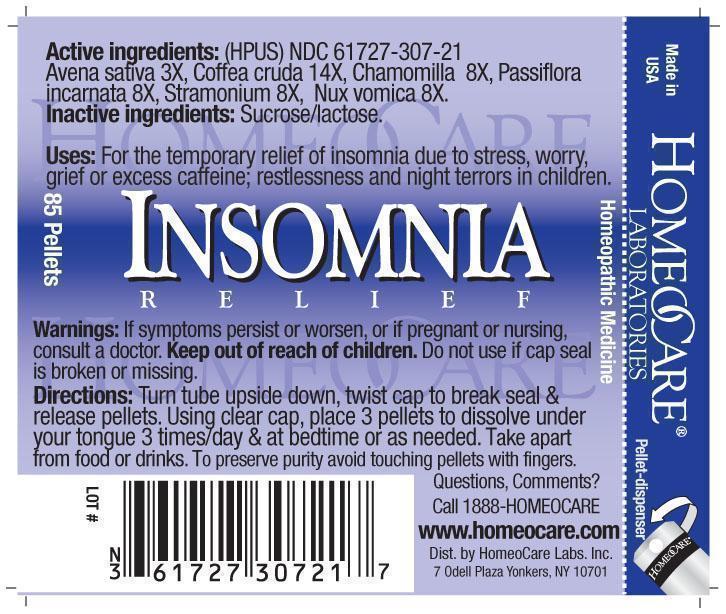 DRUG LABEL: Insomnia Relief
NDC: 61727-307 | Form: PELLET
Manufacturer: Homeocare Laboratories
Category: homeopathic | Type: HUMAN OTC DRUG LABEL
Date: 20260113

ACTIVE INGREDIENTS: AVENA SATIVA FLOWERING TOP 3 [hp_X]/4 g; ARABICA COFFEE BEAN 14 [hp_X]/4 g; MATRICARIA RECUTITA 8 [hp_X]/4 g; PASSIFLORA INCARNATA FLOWERING TOP 8 [hp_X]/4 g; DATURA STRAMONIUM 8 [hp_X]/4 g; STRYCHNOS NUX-VOMICA SEED 8 [hp_X]/4 g
INACTIVE INGREDIENTS: SUCROSE; LACTOSE

Insomnia Relief

Active Ingredients:

Avena sativa 3X, Coffea cruda 14x, Chamomilla 8X, Passiflora incarnata 8X, Stramonium 8X, Nux vomica 8X.

Purpose:

For the temporary relief of insomnia due to stress, worry, grief or excess caffeine; restlessness and night terrors in children.

Keep out of reach of children.

Indications & Usage:

Turn tube upside down, twist cap to break seal & release pellets. Using clear cap, place 3 pellets to dissolve under your tongue 3 times/day & at bedtime or as needed. Take apart from food or drinks. To preserve purity avoid touching pellets with fingers.

Warnings:

If symptoms persist or worsen, or if pregnant or nursing, consult a doctor. Keep out of reach of children. Do not use if cap seal is broken or missing.

Dosage & Administration:

Turn tube upside down, twist cap to break seal & release pellets. Using clear cap, place 3 pellets to dissolve under your tongue 3 times/day & at bedtime or as needed. Take apart from food or drinks. To preserve purity avoid touching pellets with fingers.